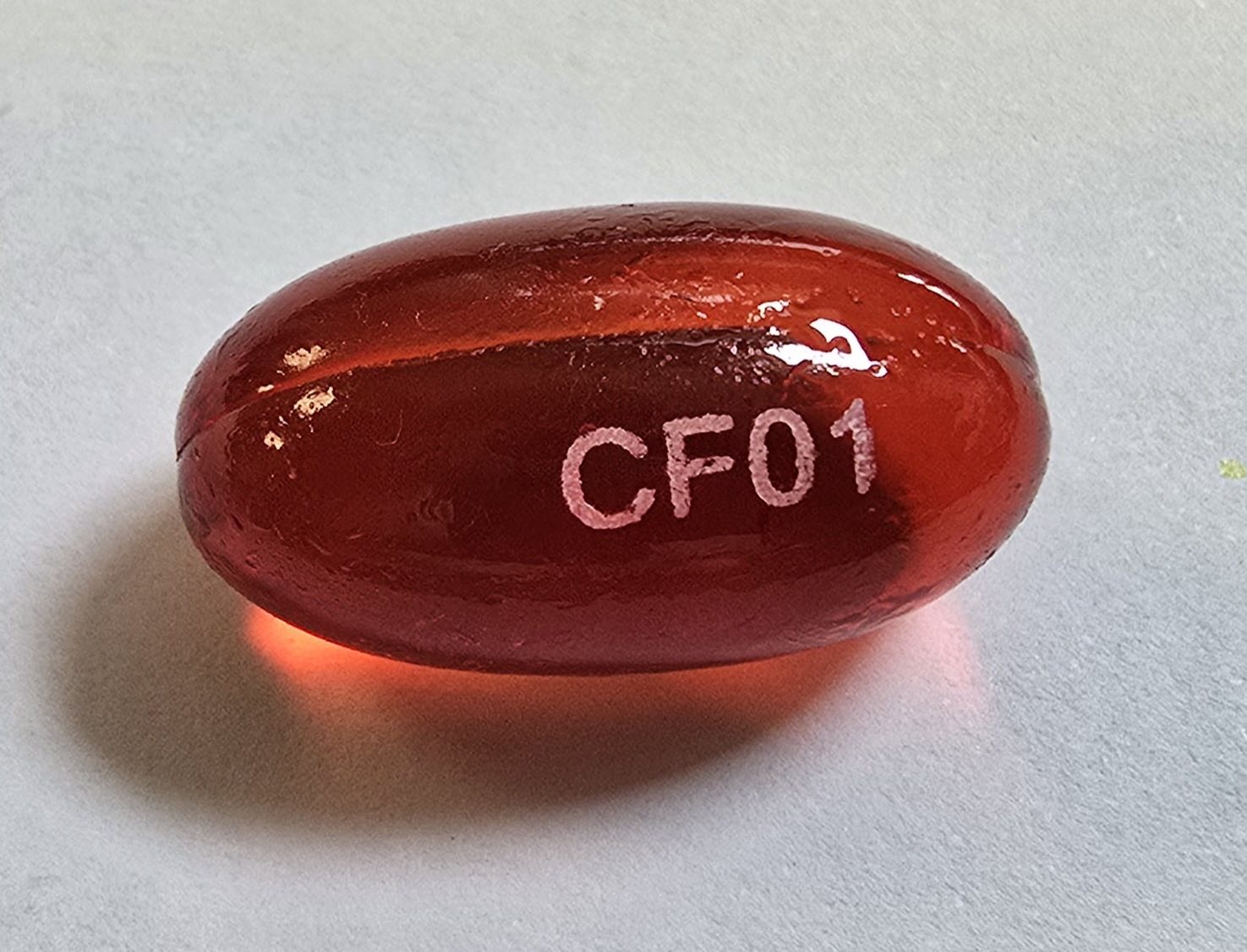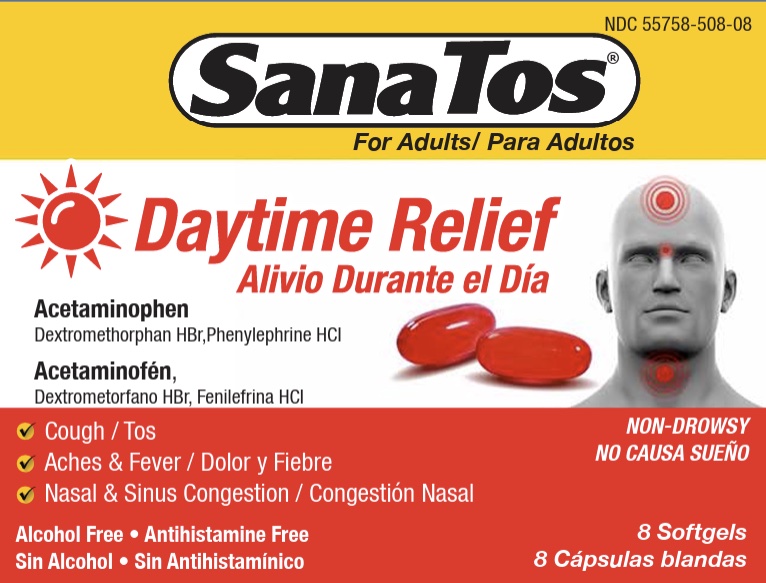 DRUG LABEL: Sanatos
NDC: 55758-508 | Form: CAPSULE, LIQUID FILLED
Manufacturer: Pharmadel LLC
Category: otc | Type: HUMAN OTC DRUG LABEL
Date: 20250808

ACTIVE INGREDIENTS: ACETAMINOPHEN 325 mg/1 1; DEXTROMETHORPHAN HYDROBROMIDE 10 mg/1 1; PHENYLEPHRINE HYDROCHLORIDE 5 mg/1 1
INACTIVE INGREDIENTS: FD&C RED NO. 40; FD&C YELLOW NO. 6; GELATIN; GLYCERIN; POLYETHYLENE GLYCOL 400; POVIDONE K30; PROPYLENE GLYCOL; WATER; SORBITOL; SORBITAN

Sanatos Daytime Softgels (HHH)

Drug Facts

.

Active ingredients and Purposes

.

PURPOSE

Active ingredients (in each softgel) | Purposes
Acetaminophen 325 mg .................... | Pain reliever/ fever reducer
Dextromethorphan HBr 10 mg ......... | Cough suppressant
Phenylephrine HCl 5 mg .................. | Nasal decongestant

Uses

Temporarily relieves cough-cold symptoms

- cough due to minor throat and bronchial irritation
- headache
- minor aches and pains
- nasal congestion
- sinus congestion and pressure
- stuffy nose
- temporarily reduces fever

Warnings

Liver warning:This product contains acetaminophen.Severe liver damage may occur if you take

- more than 8 softgels in 24 hours, which is the maximum daily
- with other drugs containing acetaminophen
- 3 or more alcoholic drinks daily while using this product

Allergy alert: Acetaminophenmay cause severe skin reactions. Symptoms may include:

- skin reddening
- blisters
- rash.

If a skin reaction occurs, stop use and seek medical help right away.

Do not use

- with any other drug containing acetaminophen (prescription or nonprescription). If you are not sure whether a drug contains acetaminophen, ask a doctor or pharmacist.
- if you are now taking a prescription monoamine oxidase inhibitor (MAOI) (certain drugs for depression, psychiatric or emotional conditions, or Parkinson's disease), or for 2 weeks after stopping the MAOI drug. If you do not know if your prescription drug contains an MAOI, ask a doctor or pharmacist before taking this product.

Ask a doctor before use if you have

- liver disease
- heart disease
- high blood pressure
- thyroid disease
- diabetes
- a cough that is accompanied by excessive phlegm (mucus)
- a persistent or chronic cough as occurs with smoking, asthma or emphysema
- difficulty urinating due to enlargement of the prostate gland

When using this product

do not exceed recommended dosage

Ask a doctor or pharmacist before use if you are

- taking the blood thinning drug warfarin

Stop use and ask a doctor if

- nervousness, dizziness, or sleeplessness occur
- pain, cough or nasal congestions gets worse or lasts more than 7 days
- fever gets worse or lasts more than 3 days
- redness or swelling is present
- new symptoms occur
- cough comes back or occurs with rash or headache that lasts.

These could be signs of a serious condition.

If pregnant or breast-feeding,

ask a health professional before use.

Keep out of reach of children.

In case of accidental overdose, get medical help or contact a Poison Control Center right away. Prompt medical attention is critical for adults as well as for children even if you do not notice any signs or symptoms.

Directions

- do not exceed 4 doses in a 24 hour period

Age | Dose
adults and children 12 years and older | 2 softgels every 4 hours, do not exceed 6 doses in a 24 hour period
children 4 to under 12 years | consult a doctor
children under 4 years | do not use

Other information

- store between 68-77°F (20-25°C)
- avoid excessive heat
- do not use if blister pack unit is punctured or torn

Inactive ingredients

FD&C red #40, FD&C yellow #6, gelatin, glycerol, polyethylene glycol 400, povidone k30, propylene glycol, sorbitol sorbitan solution, water

Questions or comments?

+1-866-359-3478(M-F) 9 AM - 5 PM EST or www.pharmadel.com

Dist by/ por:

PHARMADEL LLC

New Castle, DE 19720

www.pharmadel.com